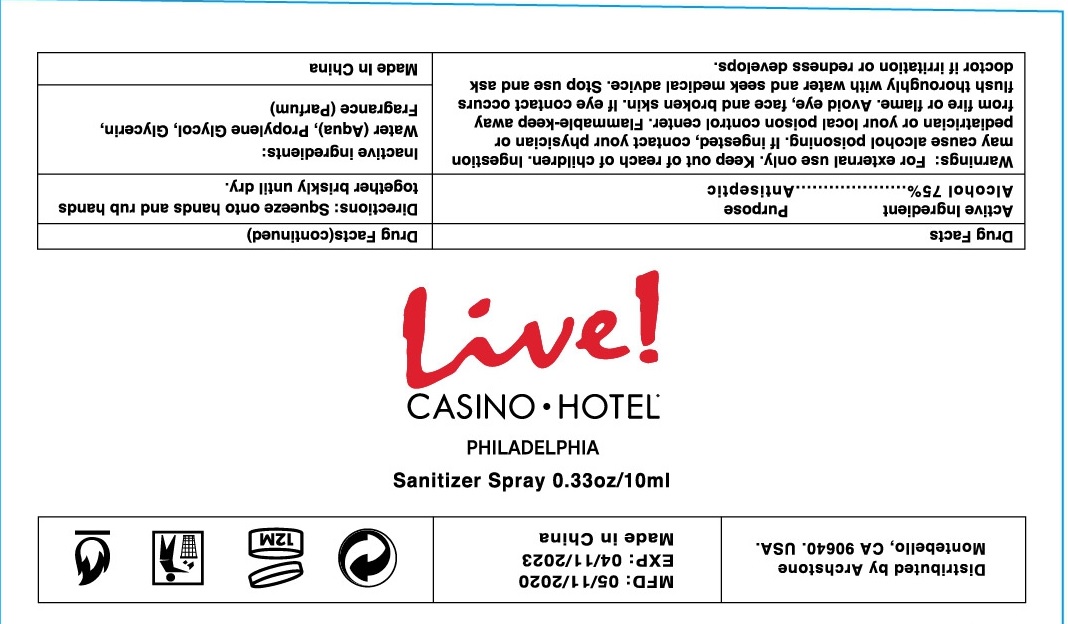 DRUG LABEL: Live Casino Hotel Sanitizer
NDC: 75531-018 | Form: SPRAY
Manufacturer: Zhejiang Ounuo Cosmetics Co., Ltd.
Category: otc | Type: HUMAN OTC DRUG LABEL
Date: 20201103

ACTIVE INGREDIENTS: alcohol 75 mL/100 mL
INACTIVE INGREDIENTS: WATER; PROPYLENE GLYCOL; GLYCERIN

Drug facts

ACTIVE INGREDIENT

Alcohol .................... 75%

PURPOSE

Antiseptic

KEEP OUT OF REACH OF CHILDREN

If swallowed, get medical help or contact a Poison Control Center right away.

INDICATIONS AND USAGE

- to decrease bacteria on the skin that could cause disease
- recommended for repeated use.

WARNINGS

For external use only
Flammable. Keep away from fire or flame.

When using this products

- Ingestion may cause alcohol poisoning. If ingested, contact your physician or pediatrician or your local poison control center.
- Avoid eye, face and broken skin. If eye contact occurs, flush thoroughy with water and seek medical advice

Stop using and ask a doctor if irritation or redness develops.

DOSAGE AND ADMINISTRATION

Squeze onto hands and rub hands together briskly until dry.

INACTIVE INGREDIENT

Water (aqua), propylene glycol, Glycerin, fragrance (parfum).